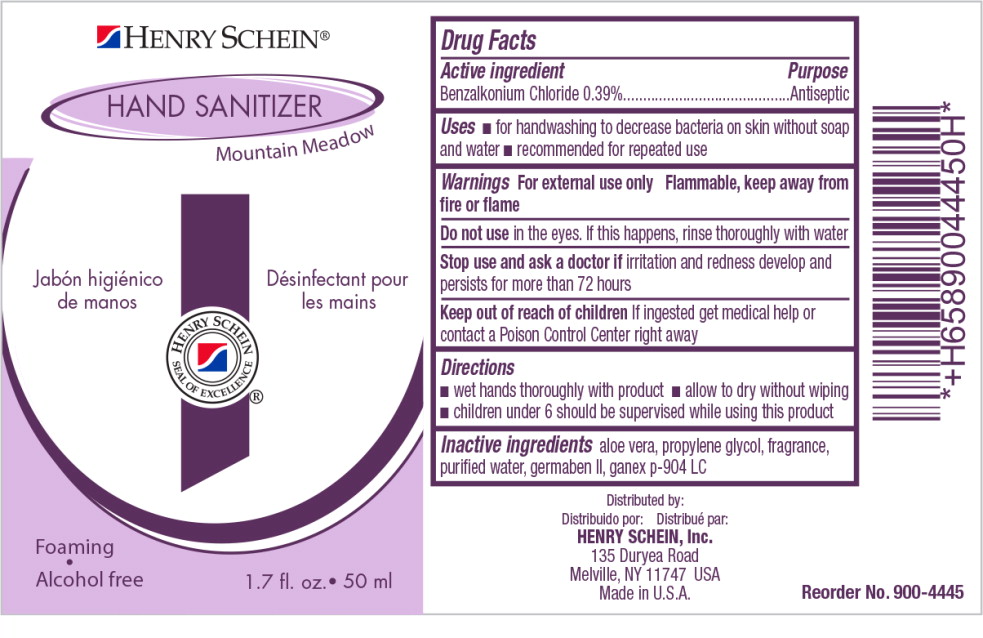 DRUG LABEL: Hand Sanitizer
NDC: 0404-4445 | Form: LIQUID
Manufacturer: Henry Schein, Inc.
Category: otc | Type: HUMAN OTC DRUG LABEL
Date: 20130130

ACTIVE INGREDIENTS: benzalkonium chloride 7.49 g/1 L
INACTIVE INGREDIENTS: water; aloe vera leaf; propylene glycol; diazolidinyl urea

Drug Facts

Active Ingredient

Benzalkonium Chloride 0.39%

Purpose

Antiseptic

Uses

- for handwashing to decrease bacteria on skin without soap and water
- recommended for repeated use

Warnings

For external use only. Flammable, keep away from fire or flame

Do not use in the eyes. If this happens, rinse thoroughly with water

Stop use and ask doctor if irritation and redness develop and persists for more than 72 hours

Keep out of reach of children

If ingested get medical help or contact a Poison Control Center right away

Directions

- wet hands thoroughly with product
- allow to dry without wiping
- children under 6 should be supervised while using this product

Inactive Ingredients

aloe vera, propylene glycol, fragrance, purified water, germaben II, ganex p-904 LC

Distributed by:

Distribuido por: Distribuépar:
HENRY SCHEIN, Inc.

135 Duryea Road
Melville, NY 11747 USA

Made in U.S.A.

PRINCIPAL DISPLAY PANEL – 50 mL Bottle Label

Henry Schein

Hand Sanitizer

Mountain Meadow
Jabón higiénico
de manos

Désinfectant pour
les mains

Foaming

Alcohol Free

1.7 fl. oz. (50 ml)